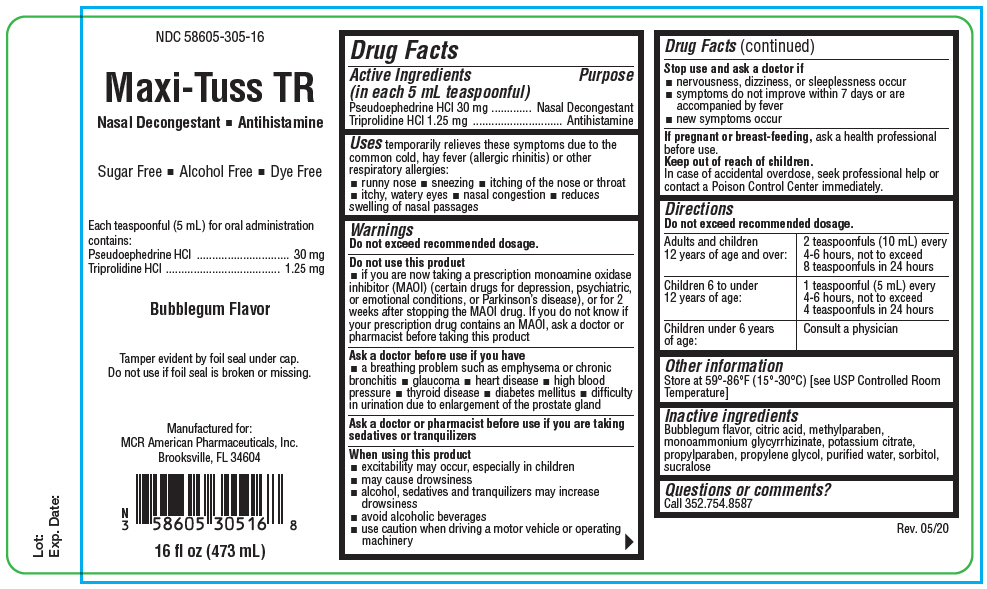 DRUG LABEL: Maxi-Tuss TR
NDC: 58605-305 | Form: LIQUID
Manufacturer: MCR American Pharmaceuticals, Inc.
Category: otc | Type: HUMAN OTC DRUG LABEL
Date: 20200623

ACTIVE INGREDIENTS: Pseudoephedrine Hydrochloride 30 mg/5 mL; Triprolidine Hydrochloride 1.25 mg/5 mL
INACTIVE INGREDIENTS: CITRIC ACID MONOHYDRATE; Methylparaben; AMMONIUM GLYCYRRHIZATE; Potassium Citrate; Propylparaben; Propylene Glycol; WATER; Sorbitol; Sucralose

Maxi-Tuss TR

Drug Facts

ACTIVE INGREDIENT

Active Ingredients (in each 5 mL teaspoonful) | Purpose
Pseudoephedrine HCl 30 mg | Nasal Decongestant
Triprolidine HCl 1.25 mg | Antihistamine

Uses

temporarily relieves these symptoms due to the common cold, hay fever (allergic rhinitis) or other respiratory allergies:

- runny nose
- sneezing
- itching of the nose or throat
- itchy, watery eyes
- nasal congestion
- reduces swelling of nasal passages

Warnings

Do not exceed recommended dosage.

Do not use this product

- if you are now taking a prescription monoamine oxidase inhibitor (MAOI) (certain drugs for depression, psychiatric, or emotional conditions, or Parkinson's disease), or for 2 weeks after stopping the MAOI drug. If you do not know if your prescription drug contains an MAOI, ask a doctor or pharmacist before taking this product

Ask a doctor before use if you have

- a breathing problem such as emphysema or chronic bronchitis
- glaucoma
- heart disease
- high blood pressure
- thyroid disease
- diabetes mellitus
- difficulty in urination due to enlargement of the prostate gland

Ask a doctor or pharmacist before use if you are taking sedatives or tranquilizers

When using this product

- excitability may occur, especially in children
- may cause drowsiness
- alcohol, sedatives and tranquilizers may increase drowsiness
- avoid alcoholic beverages
- use caution when driving a motor vehicle or operating machinery

Stop use and ask a doctor if

- nervousness, dizziness, or sleeplessness occur
- symptoms do not improve within 7 days or are accompanied by fever
- new symptoms occur

PREGNANCY OR BREAST FEEDING

If pregnant or breast-feeding, ask a health professional before use.

Keep out of reach of children.

In case of accidental overdose, seek professional help or contact a Poison Control Center immediately.

Directions

Do not exceed recommended dosage.

Adults and children 12 years of age and over: | 2 teaspoonfuls (10 mL) every 4-6 hours, not to exceed 8 teaspoonfuls in 24 hours
Children 6 to under 12 years of age: | 1 teaspoonful (5 mL) every 4-6 hours, not to exceed 4 teaspoonfuls in 24 hours
Children under 6 years of age: | Consult a physician

Other information

Store at 59°-86°F (15°-30°C) [see USP Controlled Room Temperature]

Inactive ingredients

Bubblegum flavor, citric acid, methylparaben, monoammonium glycyrrhizinate, potassium citrate, propylparaben, propylene glycol, purified water, sorbitol, sucralose

Questions or comments?

Call 352.754.8587

PRINCIPAL DISPLAY PANEL - 473 mL Bottle Label

NDC 58605-305-16

Maxi-Tuss TR

Nasal Decongestant ◾ Antihistamine

Sugar Free ◾ Alcohol Free ◾ Dye Free

Each teaspoonful (5 mL) for oral administration
contains:
Pseudoephedrine HCl
30 mg
Triprolidine HCl
1.25 mg

Bubblegum Flavor

Tamper evident by foil seal under cap.
Do not use if foil seal is broken or missing.

Manufactured for:
MCR American Pharmaceuticals, Inc.
Brooksville, FL 34604

16 fl oz (473 mL)